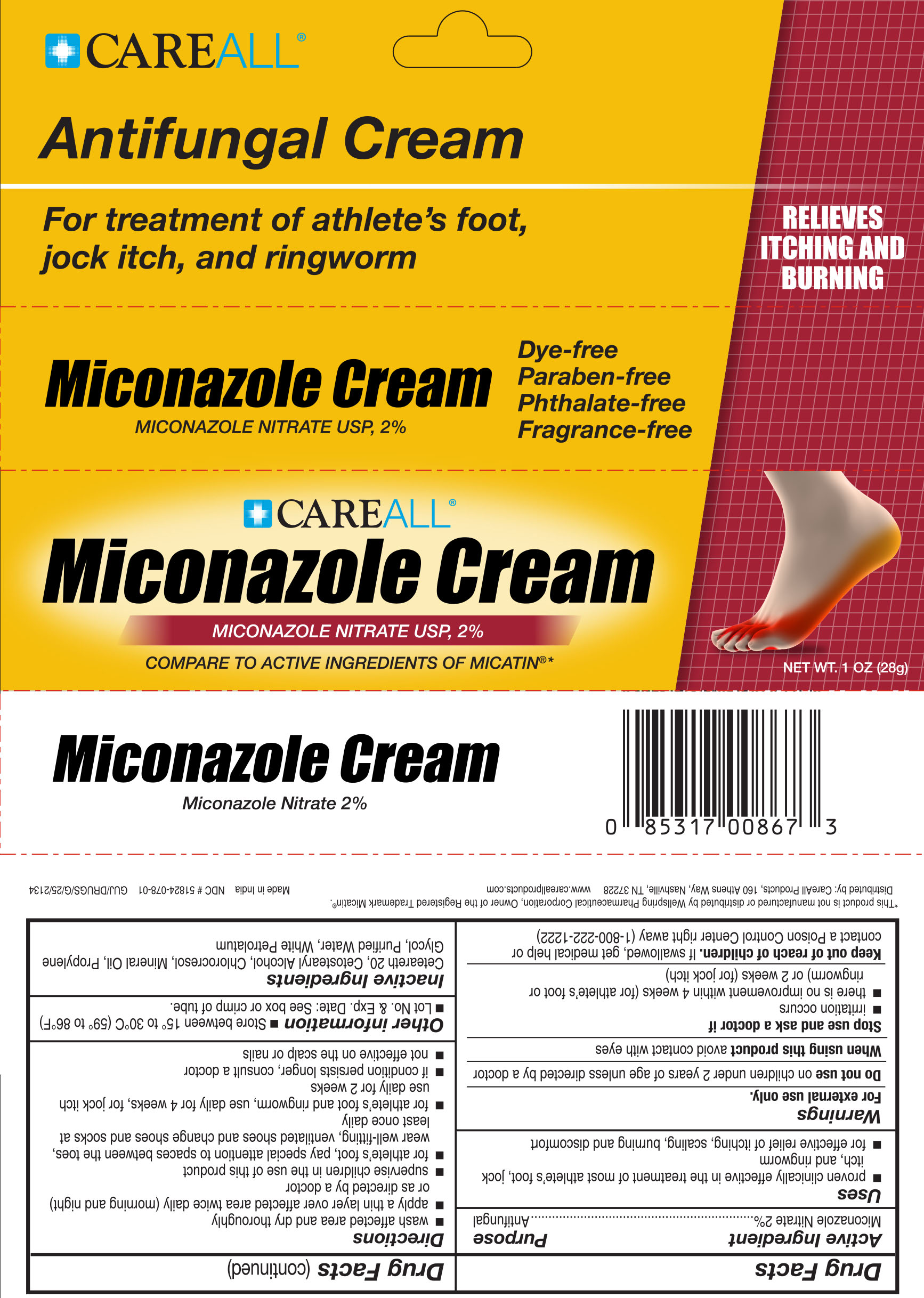 DRUG LABEL: CAREALL Miconazole Nitrate
NDC: 51824-078 | Form: CREAM
Manufacturer: New World Imports, Inc
Category: otc | Type: HUMAN OTC DRUG LABEL
Date: 20251201

ACTIVE INGREDIENTS: MICONAZOLE NITRATE 20 mg/1 g
INACTIVE INGREDIENTS: CETOSTEARYL ALCOHOL; CHLOROCRESOL; MINERAL OIL; POLYOXYL 20 CETOSTEARYL ETHER; PROPYLENE GLYCOL; WATER; WHITE PETROLATUM

Drug Facts

Active Ingredient

Miconazole Nitrate 2%

Purpose

Antifungal

Keep out of reach of children. If swallowed, get medical help or contact a Poison Control Center right away (1-800-222-1222).

Uses

- Proven clinically effective in the treatment of most athlete's foot, jock itch and ringworm.
- For effective relief of itching, scaling, burning and discomfort

Warnings

For external use only.

Do not use onchildren under 2 years of age unless directed by a doctor.

When using this productavoide contact with eyes

Stop use and ask doctor if

- irritation occurs
- there is no improvement within 4 weeks (for athlete's foot or ringworm) or 2 weeks (for jock itch)

Directions

- wash affected area and dry thoroughly
- apply a thin layer of the product over affected area twice daily (morning and night) or as directed by a doctor
- supervise children in the use of this product
- for athlete's foot, pay special attention to spaces between the toes, wear well-fitting, ventilated shoes and change shoes and socks at least once daily
- for athlete's foot and ringworm, use daily for 4 weeks, for jock itch use daily for 2 weeks
- if condition persists longer, consult a doctor
- not effective on the scalp or nails

Inactive Ingredients

Ceteareth 20, Cetostearyl Alcohol, Chlorocresol, Mineral Oil, Propylene Glycol, Purified Water, White Petrolatum